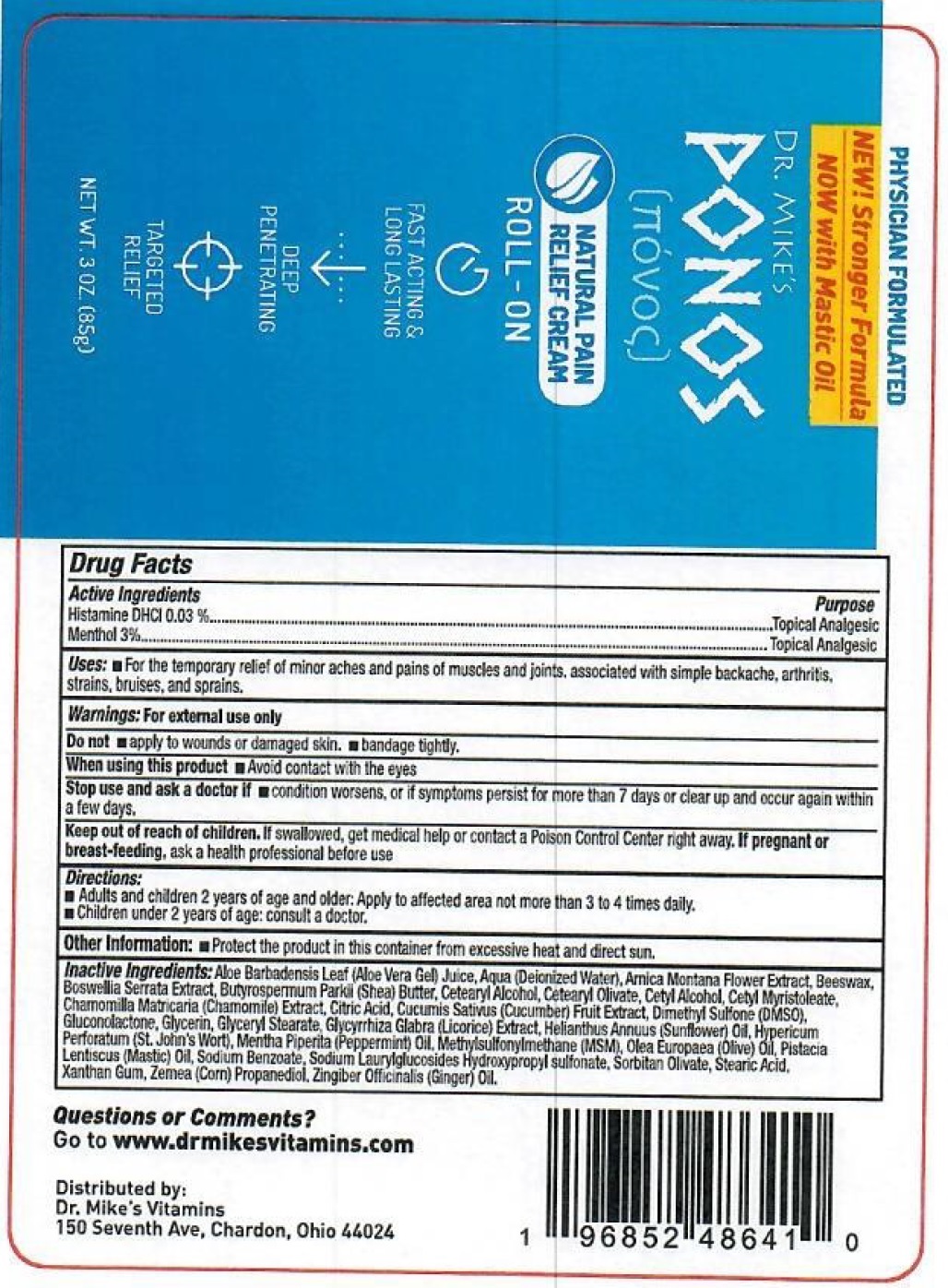 DRUG LABEL: DR. MIKES Ponos Pain Relief Cream Roll-On
NDC: 71067-359 | Form: CREAM
Manufacturer: Dr. Mike's Vitamins, LLC
Category: otc | Type: HUMAN OTC DRUG LABEL
Date: 20231105

ACTIVE INGREDIENTS: HISTAMINE DIHYDROCHLORIDE 0.3 mg/1 g; MENTHOL 30 mg/1 g
INACTIVE INGREDIENTS: ALOE VERA LEAF; WATER; YELLOW WAX; INDIAN FRANKINCENSE; SHEA BUTTER; CETOSTEARYL ALCOHOL; CETEARYL OLIVATE; CETYL ALCOHOL; CETYL MYRISTOLEATE; CHAMOMILE; CITRIC ACID MONOHYDRATE; CUCUMBER; DIMETHYL SULFONE; GLUCONOLACTONE; GLYCERIN; GLYCERYL MONOSTEARATE; GLYCYRRHIZA GLABRA; HELIANTHUS ANNUUS FLOWERING TOP; HYPERICUM PERFORATUM WHOLE; PEPPERMINT OIL; OLIVE OIL; PISTACIA LENTISCUS RESIN; SODIUM BENZOATE; SORBITAN OLIVATE; STEARIC ACID; XANTHAN GUM; CORN; GINGER

DR. MIKE'S Ponos Pain Relief Cream Roll-On

Active Ingredients

Histamine DHCl 0.03 %

Menthol 3%

Purpose

Topical Analgesic

Uses:

- For the temporary relief of minor aches and pains of muscles and joints, associated with simple backache, arthritis, strains, bruises, and sprains.

Warnings:

For external use only

• apply to wounds or damaged skin. • bandage tightly. Do not

When using this product

- Avoid contact with the eyes

Stop use and ask a doctor if

condition worsens, or if symptoms persist for more than 7 days or clear up and occur again within a few days.

Keep out of reach of children.

If swallowed, get medical help or contact a Poison Control Center right away.

If pregnant or breast-feeding,

ask a health professional before use

Directions:

- Adults and children 2 years of age and older: Apply to affected area not more than 3 to 4 times daily.
- Children under 2 years of age: consult a doctor.

Other Information:

- Protect the product in this container from excessive heat and direct sun.

Inactive Ingredients:

Aloe Barbadensis Leaf (Aloe Vera Gel) Juice, Aqua (Deionized Water), Arnica Montana Flower Extract, Beeswax, Boswellia Serrata Extract, Butyrospermum Parkii (Shea) Butter, Cetearyl Alcohol, Cetearyl Olivate, Cetyl Alcohol, Cetyl Myristoleate, Chamomilla Matricaria (Chamomile) Extract, Citric Acid, Cucumis Sativus (Cucumber) Fruit Extract, Dimethyl Sulfone (DMSO), Gluconolactone, Glycerin, Glyceryl Stearate, Glycyrrhiza Glabra (Licorice) Extract, Helianthus Annuus (Sunflower) Oil, Hypericum Perforatum (St. John's Wort), Mentha Piperita (Peppermint) Oil, Methylsulfonylmethane (MSM), Olea Europaea (Olive) Oil, Pistacia Lentiscus (Mastic) Oil, Sodium Benzoate, Sodium Laurylglucosides Hydroxypropyl sulfonate, Sorbitan Olivate, Stearic Acid, Xanthan Gum, Zemea (Corn) Propanediol, Zingiber Officinalis (Ginger) Oil.

Questions or Comments?

Go to www.drmikesvitamins.com